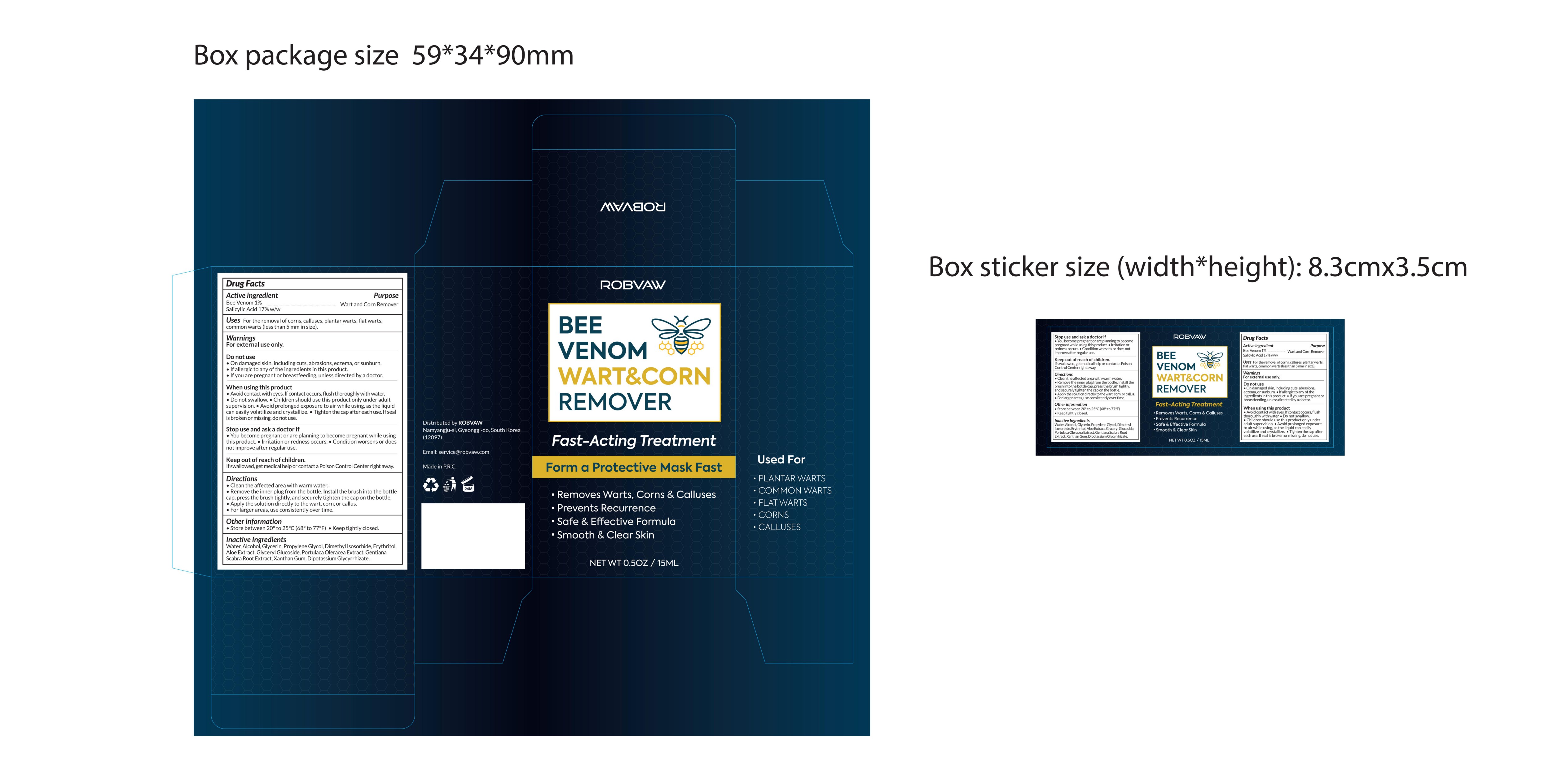 DRUG LABEL: ROBVAW BEE VENOM WART CORN REMOVER
NDC: 85817-004 | Form: LIQUID
Manufacturer: Guangzhou Qiexiran Cosmetics Co., Ltd.
Category: otc | Type: HUMAN OTC DRUG LABEL
Date: 20250927

ACTIVE INGREDIENTS: SALICYLIC ACID 17 g/100 mL; APIS MELLIFERA VENOM 1 g/100 mL
INACTIVE INGREDIENTS: ALCOHOL; ERYTHRITOL; DIMETHYL ISOSORBIDE; WATER; ALOE PERRYI LEAF; GLYCERIN; GLYCERYL GLUCOSIDE; DIPOTASSIUM GLYCYRRHIZATE; PROPYLENE GLYCOL; XANTHAN GUM; PORTULACA OLERACEA LEAF; GENTIANA SCABRA ROOT

85817-004

Active Ingredient

Salicylic Acid 17% w/w, Bee Venom 1%

Purpose

Wart and Corn Remover

Use

For the removal of corns, calluses, plantar warts, flat warts, common warts (less than 5 mm in size).

Warnings

For external use only.

Do not use

• On damaged skin, including cuts, abrasions, eczema, or sunburn. • If allergic to any of the ingredients in this product. • If you are pregnant or breastfeeding, unless directed by a doctor.

When Using

• Avoid contact with eyes. If contact occurs, flush thoroughly with water. • Do not swallow. • Children should use this product only under adult supervision. • Avoid prolonged exposure to air while using, as the liquid can easily volatilize and crystallize. • Tighten the cap after each use. If seal is broken or missing, do not use.

Stop Use

• You become pregnant or are planning to become pregnant while using this product. • Irritation or redness occurs. • Condition worsens or does not improve after regular use.

Ask Doctor

• You become pregnant or are planning to become pregnant while using this product. • Irritation or redness occurs. • Condition worsens or does not improve after regular use.

Keep Out Of Reach Of Children

If swallowed, get medical help or contact a Poison Control Center right away.

Directions

• Clean the affected area with warm water. • Remove the inner plug from the bottle. Install the brush into the bottle cap, press the brush tightly, and securely tighten the cap on the bottle. • Apply the solution directly to the wart, corn, or callus. • For larger areas, use consistently over time.

Other information

• Store between 20°to 25°C(68°to 77°F). • Keep tightly closed.

Inactive ingredients

Water, Alcohol, Glycerin, Propylene Glycol, Dimethyl Isosorbide, Erythritol, Aloe Extract, Glyceryl Glucoside, Portulaca Oleracea Extract, Gentiana Scabra Root Extract, Xanthan Gum, Dipotassium Glycyrrhizate.